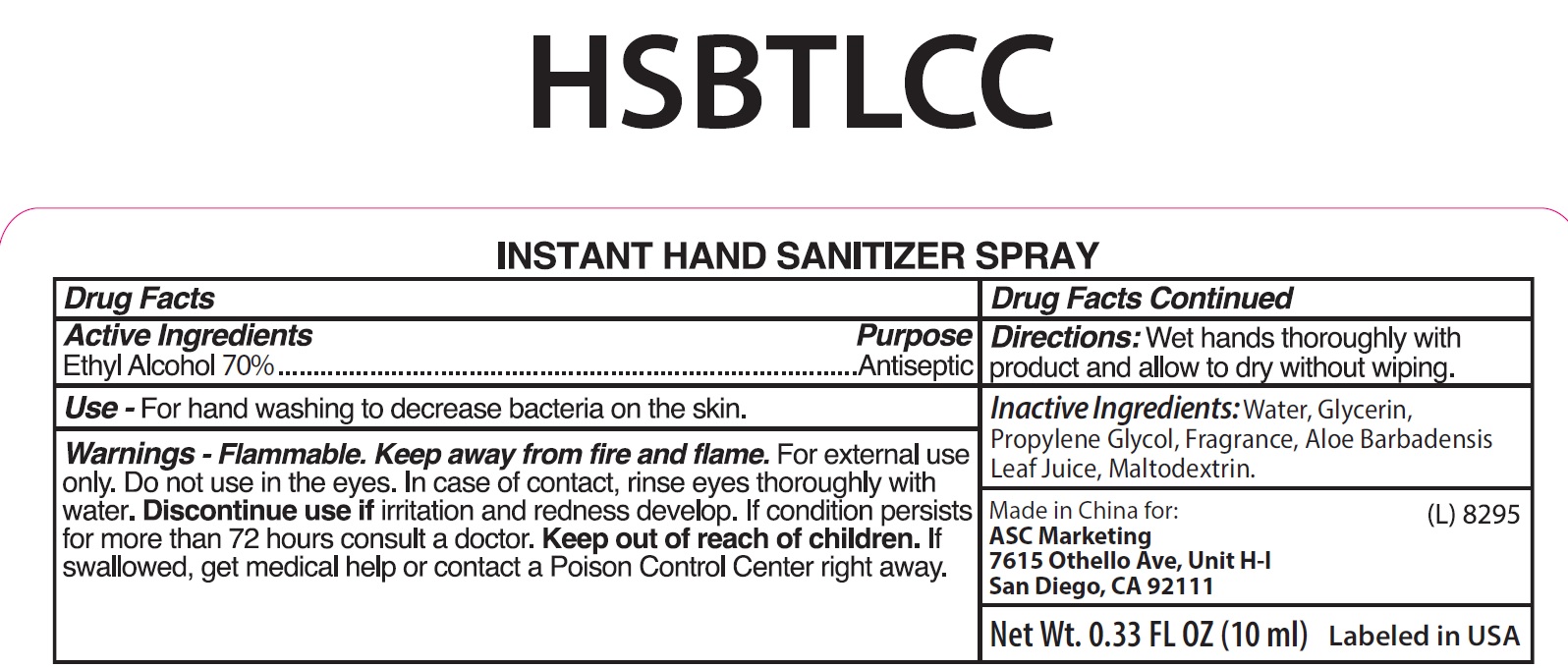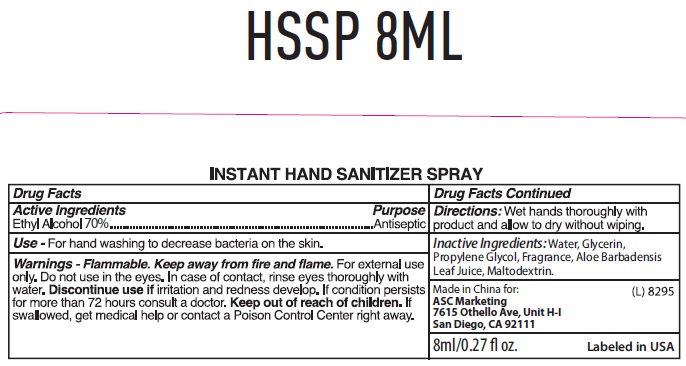 DRUG LABEL: Instant Hand Sanitizer
NDC: 73145-010 | Form: SPRAY
Manufacturer: ASC Marketing LTD
Category: otc | Type: HUMAN OTC DRUG LABEL
Date: 20231201

ACTIVE INGREDIENTS: ALCOHOL 0.7 mL/1 mL
INACTIVE INGREDIENTS: WATER; GLYCERIN; PROPYLENE GLYCOL; ALOE VERA LEAF; MALTODEXTRIN

Instant Hand Sanitizer

Active Ingredients

Ethyl Alcohol 70%

Purpose

Antiseptic

Use

For hand washing to decrease bacteria on the skin.

Warnings

For external use only. Flammable. Keep away from fire and flame.

Do not use

in the eyes. In case of contact, rinse eyes thoroughly with water. Discontinue use if irritation and redness develop. If condition persists for more than 72 hours consult a doctor.

Keep out of reach of children.

If swallowed get medical help or contact Poison Control Center right away.

Directions:

Wet hands thoroughly with product and allow to dry without wiping.

Inactive Ingredients:

Water, Glycerin, Propylene Glycol, Fragrance, Aloe Barbadensis Leaf Juice, Maltodextrin.